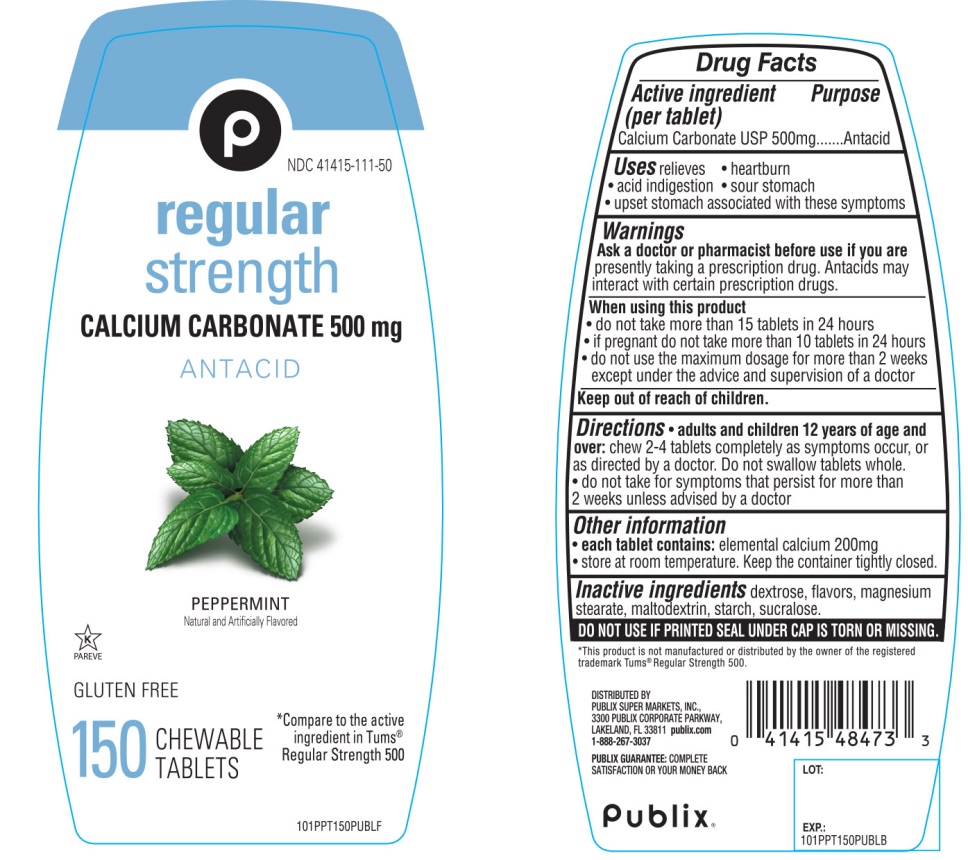 DRUG LABEL: Publix Regular Strength

NDC: 41415-111 | Form: TABLET, CHEWABLE
Manufacturer: PUBLIX SUPER MARKETS, INC
Category: otc | Type: HUMAN OTC DRUG LABEL
Date: 20251028

ACTIVE INGREDIENTS: CALCIUM CARBONATE 500 mg/1 1
INACTIVE INGREDIENTS: DEXTROSE, UNSPECIFIED FORM; MAGNESIUM STEARATE; MALTODEXTRIN; STARCH, CORN; SUCRALOSE

Publix Regular Strength Antacid Chewable Tablets 150 Count

Active ingredient (per tablet)

Calcium Carbonate USP 500mg

Purpose

Antacid

Uses

relieves

- heartburn
- acid indigestion
- sour stomach
- upset stomach associated with these symptoms

Warnings

Ask a doctor or pharmacist before use if you arepresently taking a prescription drug. Antacids may interact with certain prescription drugs.

When using this product

- do not take more than 15 tablets in 24 hours
- if pregnant do not take more than 10 tablets in 24 hours
- do not use the maximum dosage for more than 2 weeks except under the advice and supervision of a doctor.

Directions

- adults and children 12 years of age and older:chew 2-4 tablets as symptoms occur, or as directed by a doctor. Do not swallow tablets whole.
- do not take for symptoms that persist for more than 2 weeks unless advised by a doctor

Other information

- each tablet contains: elemental calcium 200mg
- store at room temperature. Keep the container tightly closed

Inactive ingredients

dextrose, flavors, magnesium stearate, maltodextrin, starch, sucralose.

Questions?

1-888-267-3037

SAFETY SEALED: DO NOT USE IF PRINTED SEAL UNDER CAP IS TORN OR MISSING

Package/Label Principal Display Panel

NDC 41415-111-50

*Compare to the active ingredient in Tum® Regular Strength 500

Publix®

regular strength

CALCIUM CARBONATE 500mg

ANTACID

PEPPERMINT

Natural and Artificially Flavored

GLUTEN FREE

150 CHEWABLE TABLETS

K PAREVE

Peppermint Flavor

DISTRIBUTED BY:

PUBLIX SUPER MARKETS, INC.,

3300 PUBLIX CORPORATE PARKWAY,

LAKELAND, FL 33811 publix.com

1-888-267-3037

PUBLIX GUARANTEE:COMPLETE SATISFACTION OR YOUR MONEY BACK

*This product is not manufactured or distributed by GlaxoSmithKline LLC, the owner of the registered trademark Tums®Regular Strength.